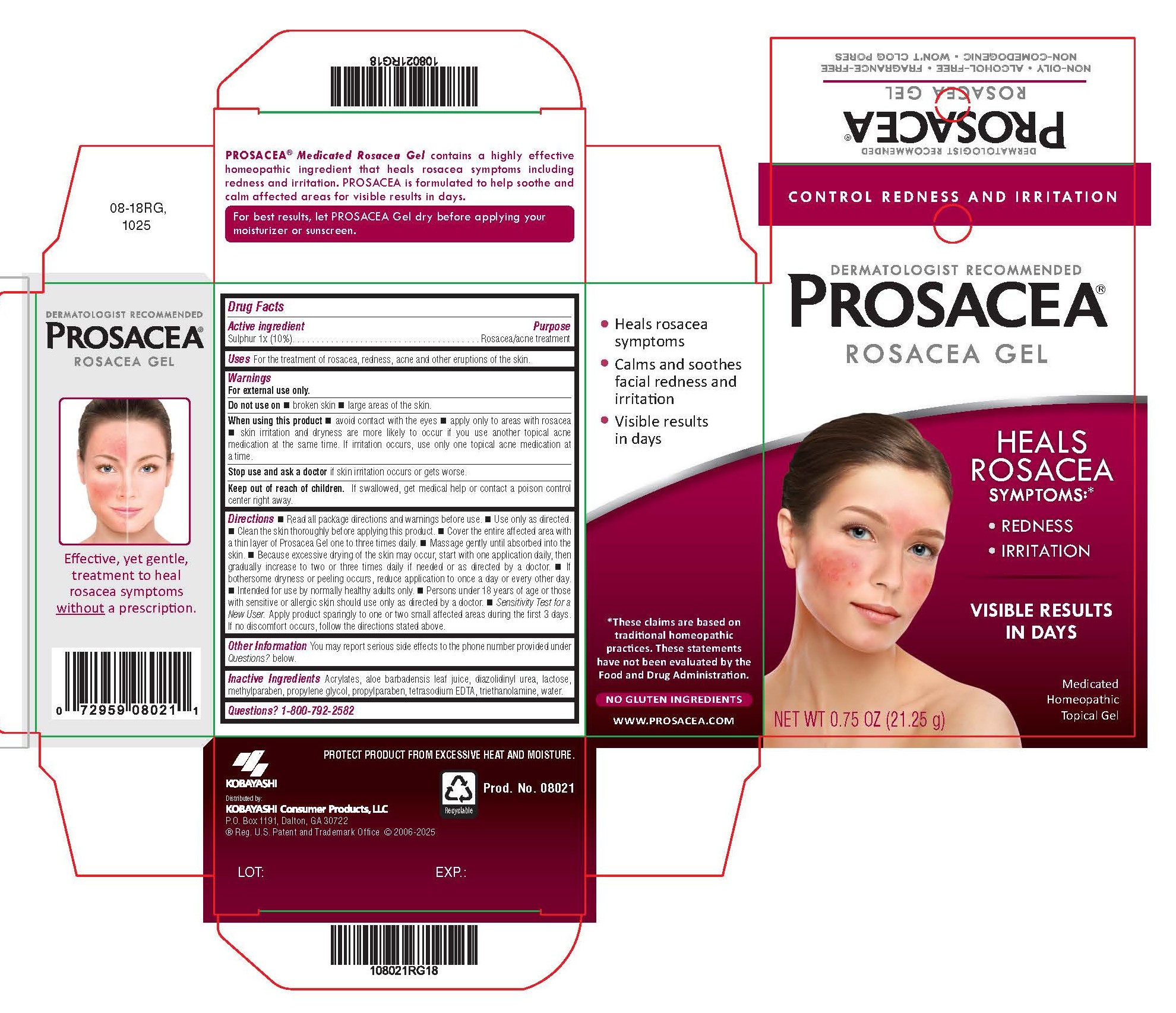 DRUG LABEL: Prosacea
NDC: 52389-173 | Form: GEL
Manufacturer: Kobayashi Healthcare International, Inc.
Category: homeopathic | Type: HUMAN OTC DRUG LABEL
Date: 20251021

ACTIVE INGREDIENTS: SULFUR 1 [hp_X]/1 g
INACTIVE INGREDIENTS: TROLAMINE; WATER; DIAZOLIDINYL UREA; EDETATE SODIUM; METHYLPARABEN; PROPYLPARABEN; CARBOMER COPOLYMER TYPE A; LACTOSE; PROPYLENE GLYCOL; ALOE VERA LEAF

Prosacea Gel

Active ingredient

Sulphur 1x (10%)

Purpose

Rosacea/acne treatment

Uses

For the treatment of rosacea, redness, acne and other eruptions of the skin.

Warnings

For external use only

Do not use on

- broken skin
- large areas of the skin

When using this product

- avoid contact with the eyes
- apply only to areas with rosacea
- skin irritation and dryness are more likely to occur if you use another topical acne medication at the same time. If irritation occurs, use only one topical acne medication at a time.

Stop use and ask a doctor if skin irritation occurs or gets worse.

Keep out of reach of children. If swallowed, get medical help or contact a poison control center right away.

Directions

- Read all package directions and warnings before use.
- Use only as directed.
- Clean the skin thoroughly before applying this product.
- Cover the entire affected area with a thin layer of Prosacea Gel one to three times daily.
- Massage gently until absorbed into the skin.
- Because excessive drying of the skin may occur, start with one application daily, then gradually increase to two or three times daily if needed or as directed by a doctor.
- If bothersome dryness or peeling occurs, reduce application to once a day or every other day.
- Intended for use by normally healthy adults only.
- Persons under 18 years of age or those with sensitive or allergic skin should use only as directed by a doctor.
- Sensitivity Test for a New User. Apply product sparingly to one or two small affected areas during the first 3 days. If no discomfort occurs, follow the directions stated above.

Other information

You may report serious side effects to the phone number provided under Questions? below.

Inactive ingredients

Acrylates, aloe barbadensis leaf juice, diazolidinyl urea, lactose, methylparaben, propylene glycol, propylparaben, tetrasodium EDTA, triethanolamine, water.

Questions? 1-800-792-2582

PATIENT INFORMATION

Dermatologist Recommended

PROSACEA®

Medicated Rosacea Gel

Heal, Don't ConcealTM, Your Rosacea Symptoms

Control Rosacea Symptoms: Redness, Pimples, Irritation

and See Visible Results in Just Days

WHAT IS ROSACEA?

Rosacea is a condition that is characterized by persistent redness and inflammation of the skin on the cheeks, nose, chin or forehead. Rosacea is generally thought to affect those with fair skin, though it can affect all skin types. Symptoms may also include acne-like bumps and visible blood vessels. Rosacea is commonly known to be aggravated by anything that causes a flushing reaction (increased blood flow) in the skin, including alcohol consumption, exposure to sun or extreme temperatures, spicy foods or other irritants. Rosacea symptoms do not typically disappear if left untreated and in some cases can worsen. Symptoms may vary among sufferers, with intermittent episodes of symptom improvement and worsening over time. Generally, rosacea progresses through three symptomatic stages:

Stage 1: In the earliest stage of rosacea, the most common symptoms can include subtle to moderate redness, stinging, burning, dryness or tightness of skin. Tiny visible blood vessels (telangiectasia) may also appear on the skin's surface. Skin may begin to react to certain cosmetics, and may also be more reactive to temperature changes or become sensitive to certain foods.

Stage 2: As the condition progresses, redness becomes more persistent. Larger areas of the face may become affected. The formation of papules (red bumps) or pustules (resembling pimples) and swelling may develop. Facial pores and sebaceous follicles may become larger and more prominent.

Stage 3: Generally, stage-3 rosacea is less common, but individuals diagnosed with this advanced stage of rosacea exhibit all characteristics of stages 1 and 2. Facial features may become thicker, irregular or even exhibit gradual deformation. Affected areas of the skin become a deeper shade of red. The sebaceous glands may be extremely enlarged, contributing to further redness, inflammation, papules, pustules and swelling of facial features. If you believe you may have rosacea, do not delay in consulting a doctor for proper diagnosis and advice.

SUGGESTIONS FOR HOW TO AVOID AND CONTROL FLARE-UPS:

Medical experts have suggested some ways to avoid aggravating symptoms which include:

1. Avoid direct sunlight as rosacea symptoms can be triggered or worsened by exposure to sunlight. When in the sun, use a mild sunscreen.
2. Avoid rubbing or scrubbing affected areas, which can irritate the skin or stimulate increased blood flow to the areas.
3. Use mild soaps, moisturizers and sunscreens and be sure to gently apply them to the face in order to avoid irritating affected areas.
4. Avoid hot drinks, spicy foods and alcoholic beverages that can cause flushing.
5. Protect your skin from extreme hot and cold conditions.
6. Avoid cosmetics, soaps, and other facial products that contain ingredients such as alcohol, menthol and fragrances.
7. Keep a log of any products, medicines, foods or weather and/or environmental conditions that may trigger flushing episodes or symptom flare-ups in order to avoid them in the future.
8. Consult your doctor for treatment recommendations.

SOME ADDITIONAL SUGGESTIONS FOR OVERALL GOOD SKIN HEALTH:

1. Get adequate rest
2. Avoid emotional stress where possible
3. Avoid excessive/stressful exercise which might cause skin flushing
4. Drink adequate amounts of water daily
5. Keep hands and face clean
6. Shampoo hair regularly using a mild antibacterial shampoo
7. Avoid touching affected areas
8. Use a broad-spectrum, SPF 25+ sunscreen and mild moisturizer daily

HOW PROSACEA® GEL CAN HELP

PROSACEA contains sulphur 1x, a medically recognized homeopathic ingredient that has been recognized for relief of common rosacea symptoms such as redness, bumps and irritation, when used as directed. PROSACEA's non-oily formula is non-comedogenic (doesn't cause pimples) and won't clog pores. It is important for successful results that once treatment is started with PROSACEA, it is continued uninterrupted, carefully following and adhering to package directions until satisfactory results are achieved or given further advice from a doctor.

For Best Results: After applying Prosacea Gel to your face, let it absorb fully into your skin before applying your moisturizer or sunscreen.

www.Prosacea.com

No Gluten Ingredients